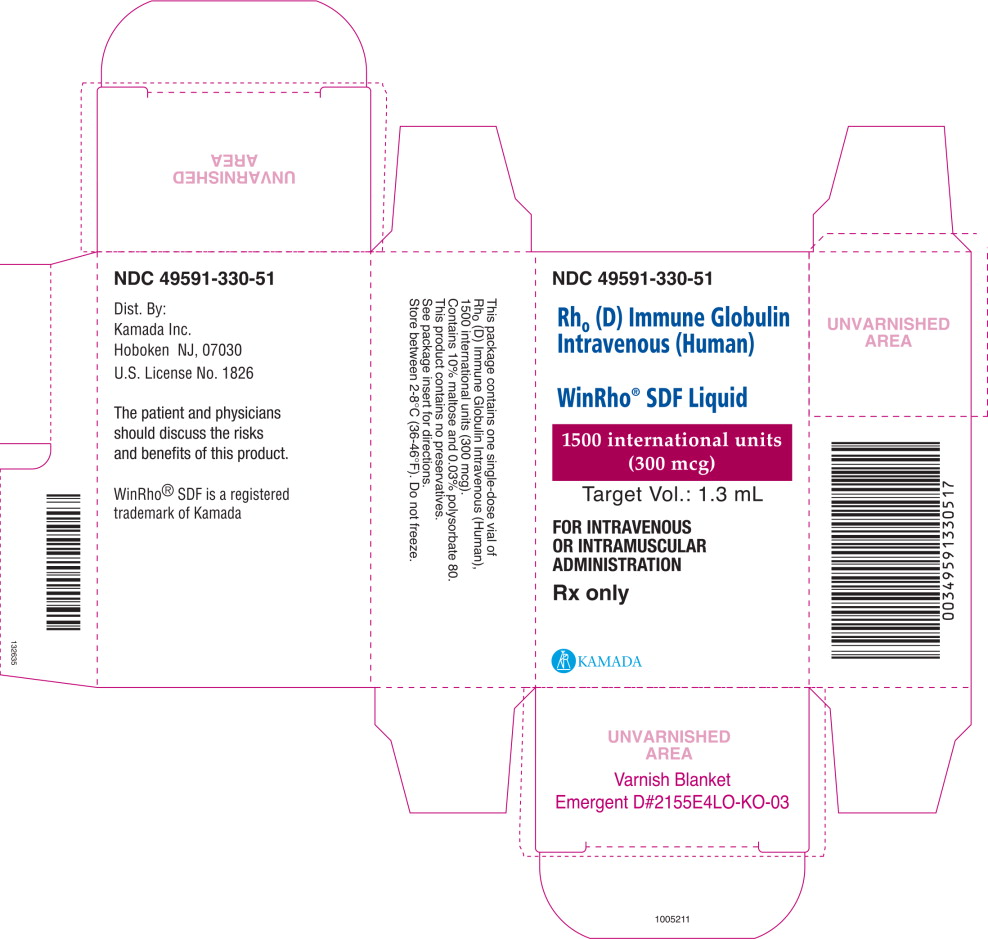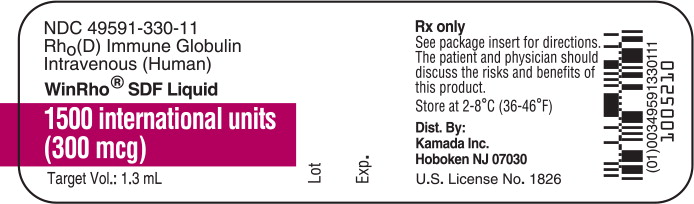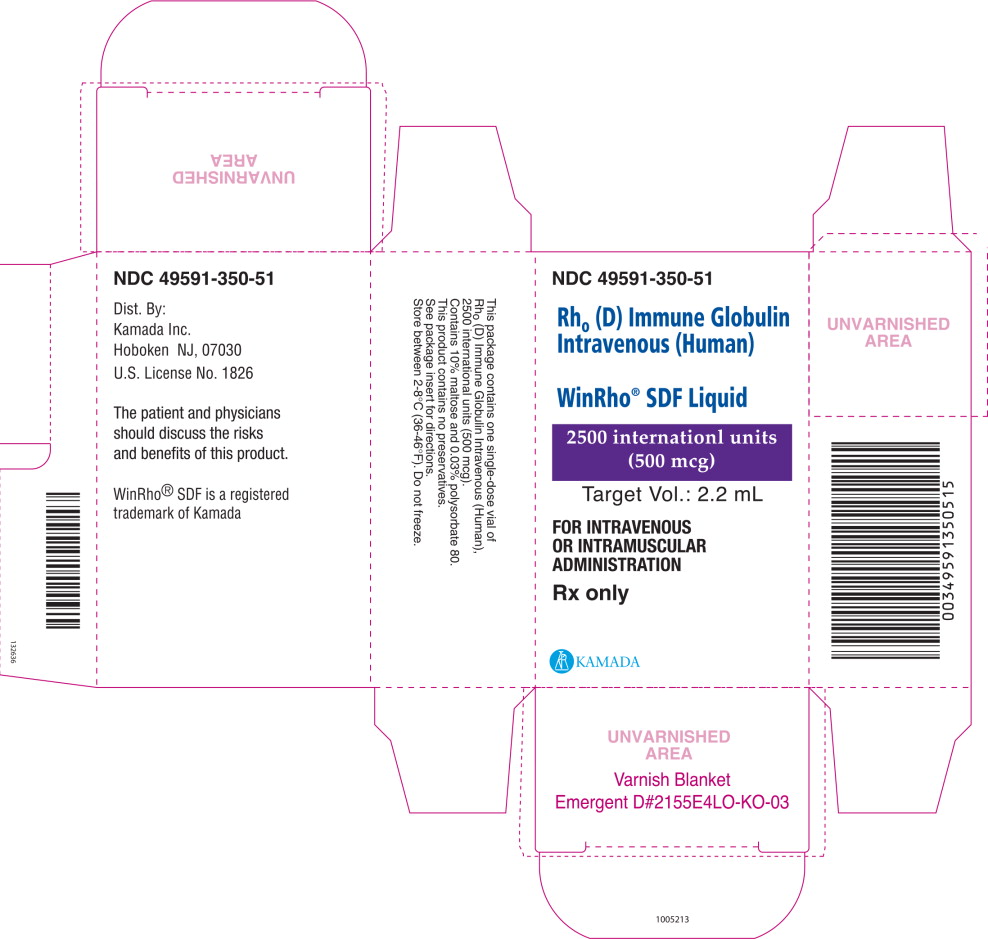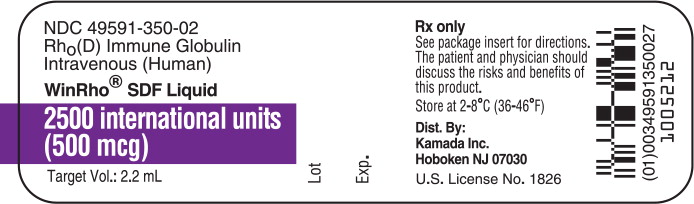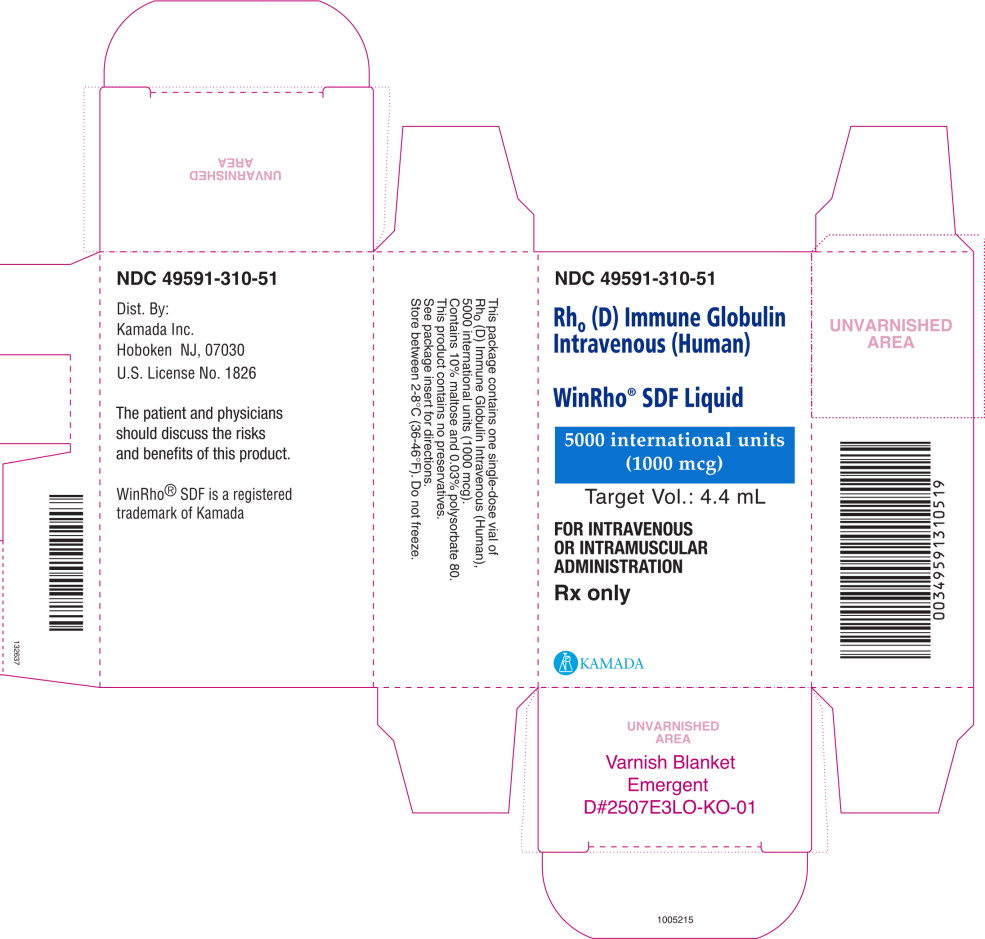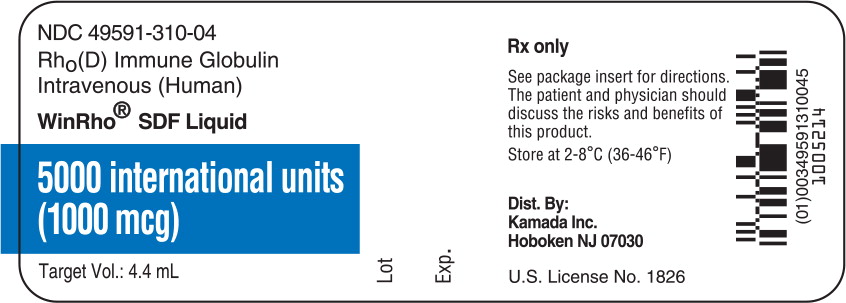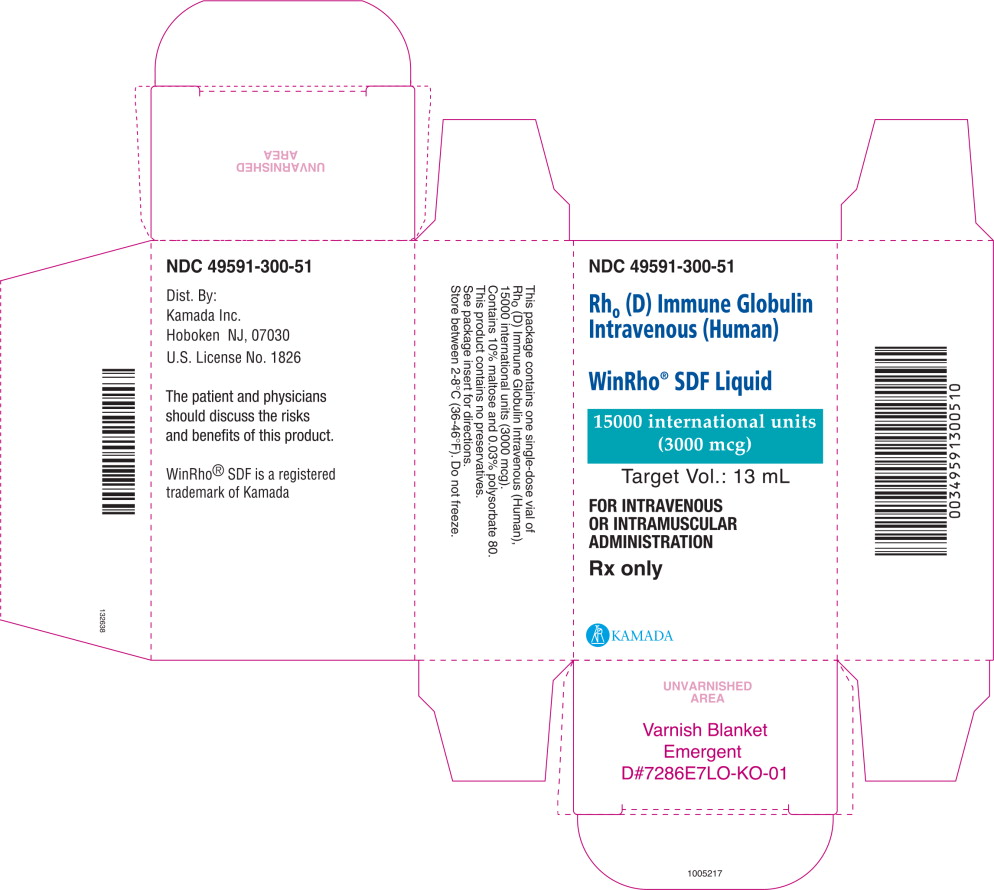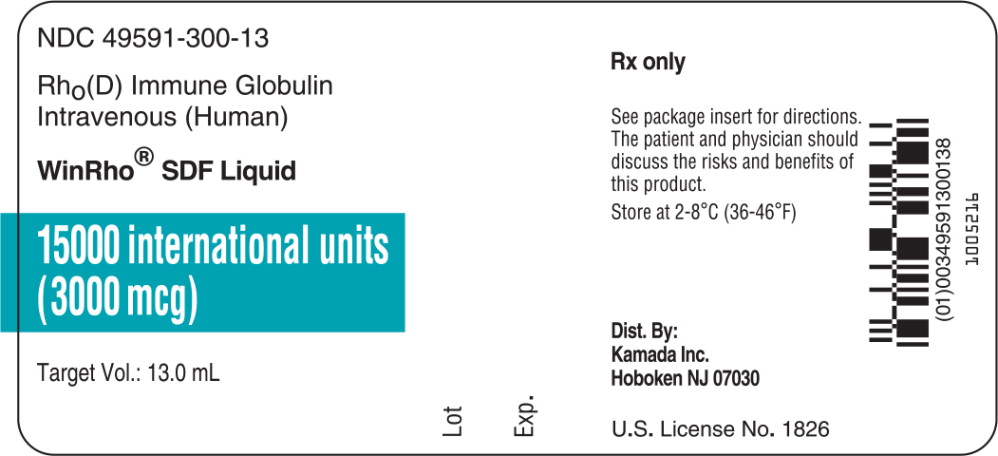 DRUG LABEL: WinRho SDF
NDC: 49591-310 | Form: INJECTION, SOLUTION
Manufacturer: Kamada Ltd.
Category: other | Type: PLASMA DERIVATIVE
Date: 20250609

ACTIVE INGREDIENTS: HUMAN RHO(D) IMMUNE GLOBULIN 5000 [iU]/4.4 mL
INACTIVE INGREDIENTS: MALTOSE, UNSPECIFIED FORM; POLYSORBATE 80

HIGHLIGHTS OF PRESCRIBING INFORMATION

These highlights do not include all the information needed to use WinRho®SDF safely and effectively. See full prescribing information for WinRho®SDF.
WinRho®SDF [Rho(D) Immune Globulin Intravenous (Human)]
Solution for Intravenous or Intramuscular Injection
Initial U.S. Approval: 1995

WARNING: INTRAVASCULAR HEMOLYSIS (IVH) IN IMMUNE THROMBOCYTOPENIC PURPURA (ITP)

See full prescribing information for complete boxed warning. This warning does not apply to Rho(D)-negative patients treated for the suppression of Rh isoimmunization.

- Intravascular hemolysis (IVH) leading to death has been reported in patients treated for ITP with WinRho® SDF.
- IVH can lead to clinically compromising anemia and multi-system organ failure including acute respiratory distress syndrome (ARDS)
- Serious complications including severe anemia, acute renal insufficiency, renal failure and disseminated intravascular coagulation (DIC) have also been reported.
- Closely monitor patients treated with WinRho® SDF for ITP in a healthcare setting for at least 8 hours after administration. Perform dipstick urinalysis to monitor for hematuria and hemoglobinuria at baseline and 2 hours, 4 hours and prior to the end of the monitoring period. Alert patients and monitor the signs and symptoms of IVH including back pain, shaking chills, fever, and discolored urine or hematuria. Absence of these signs and/or symptoms of IVH within 8 hours do not indicate IVH cannot occur subsequently. Perform post-treatment laboratory tests if signs and/or symptoms of IVH are present or suspected after WinRho® SDF administration(5.2).
- If ITP patients are to be transfused after receiving WinRho® SDF, use Rho (D)-negative red blood cells (PRBCs) so as not to exacerbate ongoing hemolysis.

1 INDICATIONS AND USAGE

WinRho® SDFis a Rho(D) Immune Globulin Intravenous (Human) indicated for:

Immune Thrombocytopenic Purpura (ITP) (1.1)

Raising platelet counts in Rho(D) positive, non-splenectomized:

- children with chronic or acute ITP
- adults with chronic ITP
- children and adults with ITP secondary to HIV infection

Suppression of Rhesus (Rh) Isoimmunization (1.2)

- Pregnancy and other obstetric conditions in non-sensitized, Rho(D)-negative women with a Rh-incompatible pregnancy including:
  - Routine antepartum and postpartum Rh prophylaxis
  - Rh prophylaxis in obstetric complications or invasive procedures
- Incompatible transfusions in Rho(D)-negative individuals transfused with blood components containing Rho(D)-positive red blood cells (RBCs).

2 DOSAGE AND ADMINISTRATION

ITP (2.1) (IV administration only)

Dose IU | Dose mcg | Rate of Administration
250 IU/kg body weight | 50 mcg/kg body weight | Single injection over 3 to 5 minutes
IU, International Units; mcg, micrograms

Suppression of Rh Isoimmunization (2.1) (IV or IM administration only)

Indication | Timing | Dose (IV or IM) | Dose (IV or IM)
Pregnancy and other obstetric conditions |  | IU (international units) | mcg (micrograms)
Routine antepartum prophylaxis | 28-weeks gestation | 1,500 IU | 300 mcg
Postpartum prophylaxis | Within 72 hours of delivery | 600 IU | 120 mcg
Threatened abortion | Immediately | 1,500 IU | 300 mcg
Amniocentesis and chorionic villus sampling before 34-weeks gestation | Immediately after procedure | 1,500 IU | 300 mcg
Abortion, amniocentesis, or other manipulation after 34-weeks gestation | Within 72 hours | 600 IU | 120 mcg
Incompatible transfusions or massive fetal hemorrhage | Within 72 hours of exposure | IV administration of 90 IU per 1 mL transfused RBC or per 2 mL transfused whole blood | IV administration of 18 mcg per 1 mL transfused RBC or per 2 mL transfused whole blood

3 DOSAGE FORMS AND STRENGTHS

WinRho®SDF is a ready to use solution in single dose vials of 600 IU (120 mcg), 1,500 IU (300 mcg), 2,500 IU (500 mcg), 5,000 IU (1,000 mcg) and 15,000 IU (3,000 mcg).

4 CONTRAINDICATIONS

- Patients with known anaphylactic or severe hypersensitivity responses to human immune globulin products. (4)
- IgA-deficient patients with antibodies to IgA or a history of hypersensitivity reaction to WinRho®SDF or any of its components. (4)
- Patients with a history of autoimmune hemolytic anemia, with pre-existing hemolysis or at high risk for hemolysis. (4)
- Infants for the suppression of Rho(D) isoimmunization. (4)

5 WARNINGS AND PRECAUTIONS

- Hypersensitivity: severe, including anaphylaxis (5.1).
- Intravascular hemolysis (IVH) with ITP treatment: hemolysis (5.3). hemolytic anemia and IVH complications (5.2). Obtain baseline labs (5.9).
- Transmissible infectious agents: e.g., viruses and, theoretically, the Creutzfeldt-Jakob disease (CJD) agent (5.4).
- Acute renal dysfunction/failure (5.5): monitor labs of those at risk (5.9).
- Thrombotic events: consider blood viscosity labs for those at risk (5.6).
- Passive transfer of antibodies may confound serologic testing. (5.7).
- Transfusion-related acute lung injury [TRALI]) (5.8): monitor for respiratory adverse events and, if they occur, test for anti-neutrophil antibodies (5.9).
- Blood glucose test monitoring interference (5.10).

6 ADVERSE REACTIONS

The most common adverse reactions occurring in ≤ 2% of doses are headache, chills, fever, asthenia, pallor, diarrhea, nausea, vomiting, arthralgia, myalgia, dizziness, malaise, hyperkinesia, abdominal or back pain, hypotension, hypertension, increased LDH, somnolence, vasodilation, pruritus, rash and sweating. (6.1)

Serious adverse reactions, such as IVH, clinically compromising anemia, acute renal insufficiency and DIC have been observed in patients receiving WinRho®SDF for treatment of ITP. Some of these cases resulted in fatal outcome. (6.2)

To report SUSPECTED ADVERSE REACTIONS, contact Kamada at 1-866-916-0077 or FDA at 1-800-FDA-1088 or www.fda.gov/medwatch.

7 DRUG INTERACTIONS

Immunoglobulin administration may transiently interfere with the immune response to live virus vaccines, such as measles, mumps and rubella. (7.1)

FULL PRESCRIBING INFORMATION

WARNING: INTRAVASCULAR HEMOLYSIS (IVH)

This warning does not apply to Rho(D)-negative patients treated for the suppression of Rh isoimmunization.

- Intravascular hemolysis (IVH) leading to death has been reported in patients treated with WinRho® SDF for immune thrombocytopenic purpura (ITP).
- IVH can lead to clinically compromising anemia and multi-system organ failure including acute respiratory distress syndrome (ARDS).
- Serious complications including severe anemia, acute renal insufficiency, renal failure and disseminated intravascular coagulation (DIC) have also been reported.
- Closely monitor patients treated with WinRho® SDF for ITP in a healthcare setting for at least 8 hours after administration. A dipstick urinalysis to monitor for hematuria and hemoglobinuria is to be performed at baseline and then after administration at 2 hours, 4 hours and prior to the end of the monitoring period. Alert patients and monitor the signs and symptoms of IVH including back pain, shaking chills, fever, and discolored urine or hemoglobinuria. Absence of these signs and/or symptoms of IVH within 8 hours do not indicate IVH cannot occur subsequently. If signs and/or symptoms of IVH are present or suspected after WinRho® SDF administration, post-treatment laboratory tests should be performed including plasma hemoglobin, haptoglobin, LDH, and plasma bilirubin (direct and indirect).
- If ITP patients are to be transfused after receiving WinRho® SDF, use Rho(D)-negative red blood cells (PRBCs) so as not to exacerbate ongoing hemolysis.

1 INDICATIONS AND USAGE

WinRho®SDF is a Rho(D) Immune Globulin Intravenous (Human) (anti-D) product that is indicated for the treatment of ITP in Rho(D)-positive patients and for the suppression of Rh isoimmunization in non-sensitized Rho(D)-negative patients.

1.1 Treatment of ITP

WinRho®SDF is indicated for use in clinical situations requiring an increase in platelet count to prevent excessive hemorrhage in the treatment of non-splenectomized, Rho(D)-positive

- children with chronic or acute ITP
- adults with chronic ITP
- children and adults with ITP secondary to HIV infection

The safety and efficacy of WinRho®SDF have not been evaluated in clinical trials for patients with non-ITP causes of thrombocytopenia or in previously splenectomized patients or in patients who are Rho(D)-negative.

1.2 Suppression of Rh Isoimmunization

Pregnancy and Other Obstetric Conditions

WinRho®SDF is indicated for the suppression of Rh isoimmunization in non-sensitized, Rho(D)-negative (D-negative) women with a Rh-incompatible pregnancy, including:

- Routine antepartum and postpartum Rh prophylaxis
- Rh prophylaxis in cases of:
  - Obstetric complication (e.g., miscarriage, abortion, threatened abortion, ectopic pregnancy or hydatidiform mole, transplacental hemorrhage resulting from antepartum hemorrhage)
  - Invasive procedures during pregnancy (e.g., amniocentesis, chorionic biopsy) or obstetric manipulative procedures (e.g., external version, abdominal trauma)

A Rh-incompatible pregnancy is assumed if the fetus/baby is either Rho(D)-positive or Rho(D)-unknown or if the father is either Rho(D)-positive or Rho(D)-unknown.

Incompatible Transfusions

WinRho®SDF is indicated for the suppression of Rh isoimmunization in Rho(D)-negative individuals transfused with Rho(D)-positive red blood cells (RBCs) or blood components containing Rho(D)-positive RBCs.

WinRho®SDF is not indicated for use as immunoglobulin replacement therapy for immune globulin deficiency syndromes.

2 DOSAGE AND ADMINISTRATION

For intravenous or intramuscular use only.

2.1 Dose

Treatment of ITP

ADMINISTER WinRho®SDF BY THE INTRAVENOUS ROUTE ONLY.

Proper care should be taken when calculating the dose of WinRho®SDF to be administered. A confusion between International Units (IU) and micrograms (mcg) of product (1 mcg = 5 IU), could result in either an overdose that could lead to a severe hemolytic reaction or a dose too low to be effective.

Since Win Rho®SDF is administered on a weight-based regimen per kilogram (kg), patient weight determination must be taken in kilograms (kg) as inappropriate use of pounds (lbs) will result in significant overdosing of WinRho®SDF.

Please note that dose for WinRho®SDF may be calculated using either international units (IU) or micrograms (mcg) per kilograms.

Table 1provides dosing guidelines for ITP patients.

Table 1: ITP Dosing Guidelines (Intravenous use only)
Indication | Initial Dose (dose in either IU or mcg) |  | Subsequent Doses (dose in either IU or mcg)
ITP (intravenous use only) | Single intravenous dose or divided doses given on two separate days |  | Determine frequency by clinical response (platelet counts, RBC, Hgb and reticulocyte count)
Hemoglobin ≥10 g/dl | 250 IU/kg | 50 mcg/kg | 250-300 IU/kg | 50-60 mcg/kg
Hemoglobin 8 to <10 g/dl (use alternative treatments for Hgb <8 g/dl) | 125-200 IU/kg | 25-40 mcg/kg | 125-200 IU/kg | 25-40 mcg/kg

- All patients should be monitored to determine clinical response by assessing platelet counts, RBCs, hemoglobin (Hgb), and reticulocyte levels [ see Warnings and Precautions (5.2) ]
- Safety and efficacy of WinRho ®SDF ®in the treatment of ITP at doses exceeding 300 IU/kg (60 mcg/kg) has not been established.
- Treatment is rarely indicated in patients with platelet count above 50x10^9/L.
- To determine the dosage and number of vials needed for the treatment of ITP:
  weight in lbs/2.21 = weight in kg
  weight in kg X selected IU (mcg) dosing level = dosage
  dosage / vial size = number of vials needed

Suppression of Rh Isoimmunization

Table 2: Rh Isoimmunization Dosing Guidelines
Indication | Initial Dose (dose in either IU or mcg) |  | Subsequent Doses (dose in either IU or mcg)
Suppression of Rh Isoimmunization (intravenous or intramuscular) | Single intravenous or intramuscular dose
Routine antepartum prophylaxis in Rh- incompatible pregnancy (28 weeks gestation) | 1,500 IU | 300 mcg
Postpartum (within 72 hours of birth of Rh0(D) positive newborn) | 600 IU | 120 mcg
Threatened abortion (immediately) | 1,500 IU | 300 mcg
Amniocentesis and chorionic villus sampling before 34 weeks gestation (immediately following procedure, then every 12 weeks during pregnancy) | 1,500 IU | 300 mcg | 1,500 IU (every 12 weeks) | 300 mcg (every 12 weeks)
Abortion, amniocentesis, or any other manipulation after 34 weeks gestation (within 72 hours) | 600 IU | 120 mcg

- If the Rh status of the baby is not known at 72 hours, administer WinRho ® SDFto the mother at 72 hours after delivery. If more than 72 hours have elapsed, administer as soon as possible up to 28 days after delivery.
- If WinRho®SDF is administered early in pregnancy for amniocentesis and chorionic villus sampling (before 34 weeks), then administer WinRho®SDF repeatedly at 12-week interval to maintain adequate levels of passively acquired anti-Rh.

Incompatible Transfusion

Table 3: Incompatible Transfusion Dosing Guidelines
Indication | Dose (dose in either IU or mcg) |  | Frequency
Incompatible Transfusion (intravenous or intramuscular) | Begin treatment within 72 hours of exposure
 | Intravenous
If exposed to Rh0(D)-Positive Whole Blood | 45 IU per ml blood | 9 mcg per ml blood |  | Every 8 hours
If exposed to Rh0(D)-Positive Red Blood Cells | 90 IU per ml cells | 18 mcg per ml cells |  | Every 8 hours
Administer this dose until total dose has been administered | 3000 IU | 600 mcg |  | Every 8 hours
 | Intramuscular
If exposed to Rh0(D)-Positive Whole Blood | 60 IU per ml blood | 12 mcg per ml blood |  | Every 12 hours
If exposed to Rh0(D)-Positive Red Blood Cells | 120 IU per ml cells | 24 mcg per ml cells |  | Every 12 hours
Administer this dose until total dose has been administered | 6000 IU | 1,200 mcg |  | Every 12 hours

For incompatible transfusion or massive fetal hemorrhage, treatment must occur within 72 hours and dose may be intravenous or intramuscular, based on the volume of blood or cells replaced.

2.2 Preparation

- Bring WinRho®SDF to room temperature prior to use.
- Inspect WinRho®SDF for particulate matter and discoloration prior to administration. Do not use if the solution is cloudy or contains particulates.
- WinRho®SDF is for single use only. Discard any unused portion.
- The solution is ready to use, no reconstitution required.
- See Table 4for the target fill volumes for each of the dosage sizes for WinRho®SDF.

Table 4: Liquid WinRho® SDF Dosage and Target Fill Volumes
Dose (IU) | Dose (mcg) | Target Fill Volume
600 IU | 120 mcg | 0.5 mL
1,500 IU | 300 mcg | 1.3 mL
2,500 IU | 500 mcg | 2.2 mL
5,000 IU | 1,000 mcg | 4.4 mL
15,000 IU | 3,000 mcg | 13.0 mL

Note:Remove the entire contents of the vial to obtain the labelled dosage of WinRho®SDF. If partial vials are required for dosage calculation, withdraw the entire contents of the vial to ensure accurate calculation of the dosage requirement. For ease in withdrawing the contents of the vial, draw back the plunger of a sterile syringe (with the needle and needle cover in place) to admit air into the syringe. Depress the plunger of the syringe to inject air into the vial. Invert vial and aspirate contents of vial into syringe.

2.3 Administration

Route of administration depends on the indication as follows:

ITP | Intravenous (IV) only
Suppression of Rh | Intravenous (IV) or intramuscular (IM)
Incompatible transfusion | Intravenous (IV) or intramuscular (IM)

ITP

- Administer the entire dose of WinRho®SDF into a suitable vein over three to five minutes.
- Administer WinRho®SDF separately from other drugs.
- If dilution of WinRho®SDF is preferred prior to intravenous administration, use onlynormal saline as diluent. Do not use Dextrose (5%) in water (D5W).

Suppression of Rh Isoimmunization

- For intravenous administration, administer WinRho®SDF separately from other drugs. WinRho®SDF should be administered at a rate of 2 mL per 5 to 15 seconds.
- For intramuscular administration, administer into the deltoid muscle of the upper arm or the anterolateral aspects of the upper thigh. Due to the risk of sciatic nerve injury, avoid the gluteal region. If the gluteal region is used, use only the upper, outer quadrant.

3 DOSAGE FORMS AND STRENGTHS

WinRho®SDF, Rho(D) Immune Globulin Intravenous (Human), is available as a ready to use solution for injection available in single dose vials of 600 IU (120 mcg), 1,500 IU (300 mcg), 2,500 IU (500 mcg), 5,000 IU (1,000 mcg) and 15,000 IU (3,000 mcg).

4 CONTRAINDICATIONS

WinRho®SDF is contraindicated in:

- Patients who have had known anaphylactic or severe systemic reaction to the administration of human immune globulin products.
- IgA-deficient patients with antibodies to IgA or a history of hypersensitivity reaction to WinRho®SDF or any of its components.
- Patients with autoimmune hemolytic anemia, with pre-existing hemolysis or at high risk for hemolysis.
- Infants for the suppression of Rho(D) isoimmunization.

5 WARNINGS AND PRECAUTIONS

5.1 Hypersensitivity

Severe hypersensitivity reactions may occur [see Contraindications(4)]. If symptoms of allergic or early signs of hypersensitivity reactions (including generalized urticaria, tightness of the chest, wheezing, hypotension, and anaphylaxis) occur, discontinue WinRho®SDF infusion immediately and institute appropriate treatment. WinRho®SDF should be administered in a setting where appropriate equipment, medication such as epinephrine, and personnel trained in the management of hypersensitivity, anaphylaxis and shock are available.

WinRho®SDF contains ≤ 40 mcg/mL IgA [see Description(11)]. Patients with antibodies to IgA have a greater risk of developing potentially severe hypersensitivity and anaphylactic reactions. WinRho®SDF is contraindicated in IgA-deficient patients with antibodies to IgA or a history of hypersensitivity reaction to WinRho®SDF or any of its components

WinRho®SDF contains 10% maltose, a disaccharide sugar derived from corn. Patients with corn allergy should avoid using WinRho®SDF due to risk of hypersensitivity. [see Contraindications(4)]

5.2 Intravascular Hemolysis (IVH) for ITP Treatment

IVH leading to death has been reported in patients treated for ITP with WinRho®SDF.

IVH can lead to clinically compromising anemia and multi-system organ failure including acute respiratory distress syndrome (ARDS).

Serious complications including severe anemia, acute renal insufficiency, renal failure and disseminated intravascular coagulation (DIC) have also been reported.^7,8

Closely monitor patients treated with WinRho®SDF for ITP in a healthcare setting for at least 8 hours after administration. Perform a dipstick urinalysis to monitor for hematuria and hemoglobinuria at baseline and then after administration at 2 hours, 4 hours and prior to the end of the monitoring period. Alert patients and monitor for signs and symptoms of IVH including back pain, shaking chills, fever, and discolored urine or hemoglobinuria. Absence of these signs and/or symptoms of IVH within eight hours do not indicate IVH cannot occur subsequently. If signs and/or symptoms of IVH are present or if IVH is suspected after WinRho®SDF administration, perform post-treatment laboratory tests including plasma hemoglobin, haptoglobin, LDH, and plasma bilirubin (direct and indirect).

5.3 Hemolysis for ITP Treatment

Although the mechanism of action of WinRho®SDF in the treatment of ITP is not completely understood it is postulated that anti-D binds to the Rho(D) RBC resulting in formation of antibody-coated RBC complexes. Immune-mediated clearance of the antibody-coated RBC complexes would spare the antibody-coated platelets because of the preferential destruction of antibody-coated RBC complexes by the macrophages located in the reticuloendothelial system.^9-11The side effect of this action is a decrease in hemoglobin levels (extravascular hemolysis).^7The pooled data from ITP clinical studies demonstrated a mean decrease from baseline in hemoglobin levels of 1.2 g/dL within 7 days after administration of WinRho®SDF.

In patients with pre-disposing conditions, renal and cardiovascular complications of IVH may occur more frequently. Patients of advanced age (age over 65 years) with co-morbid conditions may be at an increased risk of developing sequelae from acute hemolytic reactions. If a patient has evidence of hemolysis (reticulocytosis greater than 3%) or is at high risk for hemolysis [positive direct antiglobulin test (DAT) not attributed to previous immune globulin administration], alternate therapies must be used.

If the patient has lower than normal hemoglobin levels (less than 10 g/dL), a reduced dose of 125 to 200 IU/kg (25 to 40 mcg/kg) should be given to minimize the risk of increasing the severity of anemia in the patient. Alternative treatments should be used in patients with hemoglobin levels that are less than 8 g/dL due to the risk of increasing the severity of the anemia [see Dose (2.1) ].

Significant anemia may present with pallor, hypotension, or tachycardia while acute renal insufficiency may present with oliguria or anuria, edema and dyspnea. Patients with IVH who develop DIC may exhibit signs and symptoms of increased bruising and prolongation of bleeding time and clotting time which may be difficult to detect in the ITP population. Consequently, the diagnosis of this serious complication of IVH is dependent on laboratory testing [see Warnings and Precautions(5.9)]. Previous uneventful administration of WinRho®SDF does not preclude the possibility of an occurrence of IVH and its complications following any subsequent administration of WinRho®SDF. Have confirmatory laboratory testing on ITP patients presenting with signs and/or symptoms of IVH and its complications after anti-D administration [see Warnings and Precautions(5.9)]

If ITP patients are to be transfused, use Rho(D)-negative red blood cells (PRBCs) so as not to exacerbate ongoing hemolysis.

5.4 Transmissible Infectious Agents

Because WinRho®SDF is made from human plasma; it may carry a risk of transmitting infectious agents, e.g., viruses and theoretically, the Creutzfeldt-Jakob disease (CJD) agent. The risk of transmitting an infectious agent has been reduced by screening plasma donors for prior exposure to certain pathogens, testing for the presence of certain current viral infections, and including virus inactivation/removal steps in the manufacturing process [see Description(11)].

Report all infections thought to have been transmitted by WinRho®SDF to Kamada at 1-866-916-0077. The physician should discuss the risks and benefits of this product with the patient.

5.5 Acute Renal Insufficiency/Failure

Acute renal insufficiency/failure, osmotic nephropathy, acute tubular necrosis, proximal tubular nephropathy, and death may occur upon use of Immune Globulin Intravenous (IGIV) products, including WinRho®SDF.^2Ensure that patients are not volume depleted before administering WinRho®SDF. For patients at risk of renal insufficiency or failure, including those with any degree of pre-existing renal insufficiency, diabetes mellitus, advanced age (above 65 years of age), volume depletion, sepsis, paraproteinemia, or receiving known nephrotoxic drugs, administer WinRho®SDF at the minimum infusion rate practicable and assess renal function, including measurement of blood urea nitrogen (BUN) and serum creatinine, before the initial infusion of WinRho®SDF and at appropriate intervals thereafter.

5.6 Thromboembolic Events

Thromboembolic events may occur during or following treatment with WinRho®SDF and other IGIV products.^3,4Patients at risk include those with a history of atherosclerosis, multiple cardiovascular risk factors, advanced age, impaired cardiac output, coagulation disorders, prolonged periods of immobilization, history of arterial or venous thrombosis, estrogen use, indwelling central vascular catheters, and/or known/suspected hyperviscosity. Thrombosis may occur in the absence of known risk factors.

Consider baseline assessment of blood viscosity in patients at risk for hyperviscosity including those with cryoglobulins, fasting chylomicronemia/markedly high triacylglycerols (triglycerides), or monoclonal gammopathies. For patients who are at risk of developing thromboembolic events, administer WinRho®SDF at the minimum rate of infusion practicable.

5.7 Interference with Serological Testing

After administration of WinRho®SDF, a transitory increase of various passively transferred antibodies in the patient's blood may yield positive serological testing results, with the potential for misleading interpretation. Passive transmission of antibodies to erythrocyte antigens (e.g., A, B, C and E) and other blood group antibodies [for example, anti Duffy, anti Kidd (anti JKa) antibodies]^5may cause a positive direct or indirect (Coombs') test.

A large fetomaternal hemorrhage late in pregnancy or following delivery may cause a weak mixed field positive Dutest result. Assess such an individual for a large fetomaternal hemorrhage and adjust the dose of WinRho®SDF accordingly. The presence of passively administered anti Rho(D) in maternal or fetal blood can lead to a positive direct Coombs' test. If there is an uncertainty about the father's Rh group or immune status, administer WinRho®SDF to the mother.

5.8 Transfusion-Related Acute Lung Injury (TRALI)

Non-cardiogenic pulmonary edema may occur in patients following IGIV treatment, including WinRho®SDF.^6TRALI is characterized by severe respiratory distress, pulmonary edema, hypoxemia, normal left ventricular function, and fever. Symptoms typically appear within 1 to 6 hours following administration of blood products.

Monitor patients for pulmonary adverse reaction. If TRALI is suspected, perform appropriate tests for the presence of anti-neutrophil antibodies and anti-HLA antibodies in both the product and patient serum. TRALI may be managed using oxygen therapy with adequate ventilatory support.

5.9 Monitoring: Laboratory Tests

- For all ITP patients, blood type, blood count, reticulocyte count, DAT and dipstick urinalysis are recommended before deciding to treat patients with WinRho®SDF. In patients with evidence of hemolysis (reticulocytosis greater than 3%), or patients at risk of hemolysis (positive DAT not attributed to previous immune globulin administration) use other treatments.^1
- Closely monitor patients administered WinRho®SDF for at least 8 hours post administration and perform a dipstick urinalysis to monitor for hematuria and hemoglobinuria at baseline and then after administration at 2 hours, 4 hours and prior to the end of the monitoring period.
- If signs and/or symptoms of IVH and its complications are present after anti-D administration, perform appropriate confirmatory laboratory testing including, but not limited to, CBC (i.e. hemoglobin, platelet counts), haptoglobin, plasma hemoglobin, urine dipstick, assessment of renal function (i.e. BUN, serum creatinine), liver function (i.e. LDH, direct and indirect bilirubin) and DIC specific tests such as D-dimer or Fibrin Degradation Products (FDP) or Fibrin Split Products (FSP).
- Periodic monitoring of renal function and urine output in patients who are at increased risk of developing acute renal failure [see Warnings and Precautions(5.5)]. Assess renal function in these at-risk patients, including measurement of BUN and serum creatinine, before the initial infusion of WinRho® SDF and at appropriate intervals thereafter.
- If TRALI is suspected in ITP patients, perform appropriate tests for the presence of anti-neutrophil antibodies in both the product and patient serum [see Warnings and Precautions(5.9)].

5.10 Interference with Blood Glucose Testing: False High Blood Glucose Levels

The liquid formulation of WinRho®SDF contains maltose. Maltose in IGIV products has been shown to give falsely high blood glucose levels in certain types of blood glucose testing systems [for example, by systems based on glucose dehydrogenase pyrroloquinolinequinone (GDH-PQQ) or glucose-dye-oxidoreductase methods]. Due to the potential for falsely elevated glucose readings, only use testing systems that are glucose-specific to test or monitor blood glucose levels in patients receiving maltose-containing parenteral products, including WinRho®SDF Liquid.

Carefully review the product information of the blood glucose testing system, including that of the test strips, to determine if the system is appropriate for use with maltose-containing parenteral products. If any uncertainty exists, contact the manufacturer of the testing system to determine if the system is appropriate for use with maltose-containing parenteral products.

5.11 Suppression of Rh Isoimmunization

Do not administer WinRho®SDF to Rho(D)-negative individuals who are Rh immunized as evidenced by an indirect antiglobulin (Coombs') test revealing the presence of anti-Rho(D) (anti-D) antibody. For postpartum use following a Rh-incompatible pregnancy administer WinRho®SDF to the mother only. Do not administer to the newborn infant.

6 ADVERSE REACTIONS

Serious adverse reactions, some of these cases resulted in fatal outcome, have been observed in patients receiving WinRho® SDF for the treatment of ITP. These include: intravascular hemolysis (IVH), clinically compromising anemia, acute renal insufficiency and DIC [see Adverse Reactions, (6.2)].

The most common adverse reactions observed for allindications are: headache, chills, fever, asthenia, pallor, diarrhea, nausea, vomiting, arthralgia, myalgia, dizziness, hyperkinesia, abdominal or back pain, hypotension, hypertension, increased LDH, somnolence, vasodilation, pruritus, rash and sweating. All adverse reactions listed occurred in ≤ 2% of WinRho®SDF doses administered in clinical trials.

Adverse reactions observed in the use of WinRho®SDF for Suppression of Rh Isoimmunization are < 0.1% in Rho(D)-negative individuals.

6.1 Clinical Trials Experiences

Because clinical studies are conducted under different protocols and widely varying conditions, adverse reaction rates observed in the clinical trials of a specific drug product cannot be directly compared to rates in clinical trials of another drug, and may not reflect rates observed in practice.

Treatment of ITP

The safety of WinRho®SDF was evaluated in clinical trials (n=161) in children and adults with acute and chronic ITP and adults and children with ITP secondary to HIV. Overall, 417 adverse events were reported by 91 patients (57%). The most common adverse events were headache (14% of the patients), fever (11% of the patients) and asthenia (11% of the patients). A total of 117 adverse drug reactions were reported by 46 patients (29%). Headache, chills, and fever were the most common related adverse events (Table 5). With respect to safety profile per administration, 60/848 (7%) of WinRho®SDF infusions had at least one adverse reaction. The most common adverse reactions were headache (19 infusions; 2%), chills (14 infusions; < 2%), and fever (9 infusions; 1%).

Table 5: Adverse Drug Reactions with an Incidence ≥ 5% of Patients
Body System | Adverse Event | All Studies | Children | Adults
Body System | Adverse Event | # of Patients (%)
Body as a Whole | Headache | 18 (11) | 8 (11) | 10 (12)
Body as a Whole | Chills | 13 (8) | 4 (5) | 9 (10)
Body as a Whole | Fever | 9 (6) | 5 (7) | 4 (5)
Body as a Whole | Asthenia | 6 (4) | 2 (3) | 4 (5)
Body as a Whole | Infection | 4 (3) | 4 (5) | 0 (0)
Nervous System | Dizziness | 6 (4) | 2 (3) | 4 (5)

In four clinical trials of patients treated with the recommended initial intravenous dose of 250 IU/kg (50 mcg/kg), the mean maximum decrease in hemoglobin was 1.70 g/dL (range: +0.40 to -6.1 g/dL). At a reduced dose, ranging from 125 to 200 IU/kg (25 to 40 mcg/kg), the mean maximum decrease in hemoglobin was 0.81 g/dL (range: +0.65 to -1.9 g/dL). Only 5/137 (3.7%) of patients had a maximum decrease in hemoglobin of greater than 4 g/dL (range: -4.2 to -6.1 g/dL).

Suppression of Rh Isoimmunization

In the clinical trial of 1,186 Rho(D)-negative pregnant women, no adverse reactions were reported to Rho(D) IGIV.

6.2 Post-marketing Experience

The following adverse reactions listed by body system have been identified during the post-approval use of WinRho®SDF. Because post-marketing adverse reactions are reported voluntarily from a population of uncertain size, it is not always possible to reliably estimate their frequency or establish a causal relationship to product exposure.

Intravascular hemolysis (IVH) leading to death has been reported in patients treated with WinRho® SDF for immune thrombocytopenic purpura (ITP).

Serious complications including severe anemia, acute renal insufficiency, renal failure and disseminated intravascular coagulation (DIC) have also been reported.

Blood and Lymphatic: | Intravascular hemolysis, disseminated Intravascular coagulation, hemoglobinemia
Cardiac: | Cardiac arrest, cardiac failure, myocardial infarction, tachycardia
Gastrointestinal: | Nausea
General: | Chest pain, fatigue, edema, pain
Hepatobilliary: | Jaundice
Immune System: | Anaphylactic reaction/shock, hypersensitivity, injection site reaction including induration, pruritus and/or swelling
Musculoskeletal: | Myalgia, muscle spasm, pain in extremities
Renal: | Renal failure, anuria, chromaturia, hematuria, hemoglobinuria
Respiratory: | Acute respiratory distress syndrome, dyspnea, transfusion related acute lung injury
Skin: | Hyperhidrosis, pruritus, rash

Healthcare professionals should report serious adverse reactions following the administration of WinRho®SDF to Kamada at 1-866-916-0077 or FDA's MedWatch reporting system by phone (1-800-FDA-1088).

7 DRUG INTERACTIONS

7.1 Live Virus Vaccines

Administration of WinRho®SDF concomitantly with other drugs has not been evaluated. Passive transfer of antibodies may transiently impair the immune response to live attenuated virus vaccines such as measles, mumps, rubella, and varicella (see Patient Counseling Information[ 17.1]). Do not give immunization with live vaccines within 3 months after WinRho®SDF administration.

8 USE IN SPECIFIC POPULATIONS

8.1 Pregnancy

Risk Summary

For the treatment of ITP, there is no human data or animal data available to establish the presence or absence of drug-associated risk.

When administered to pregnant women in a clinical trial to evaluate WinRho®SDF for suppression of Rh isoimmunization [ see Clinical Studies(14.2)] following dosing regimens similar to Table 2[ see Dosing and Administration(2.1)], WinRho®SDF was not shown to harm the fetus or newborn.^12

8.2 Lactation

Risk Summary

There is no information regarding the presence of WinRho®SDF in human milk, the effect on the breastfed infant, and the effects on milk production. The developmental and health benefits of breastfeeding should be considered along with the mother's clinical need for WinRho®SDF and any potential adverse effects on the breastfed infant from WinRho®SDF or from the underlying maternal condition.

8.4 Pediatric Use

The safety and effectiveness of WinRho®SDF has been evaluated for the treatment of chronic or acute ITP in children and in children (<16 years of age) with ITP secondary to HIV infection [see Adverse Reactions(6.2)]. The dosing recommendation in the treatment of children with ITP is the same as in adults [see Dosage and Administration(2.1)].

8.5 Geriatric Use

Clinical studies of WinRho®SDF did not include sufficient numbers of subjects aged 65 and over to determine whether they respond differently from younger subjects. Post marketing clinical experience suggests that patients of advanced age (age over 65) with co-morbid conditions including but not limited to cardio-respiratory decompensation, renal failure or insufficiency or prothrombotic conditions are at increased risk of developing serious complications from acute hemolytic reactions such as IVH. Patients receiving doses in excess of 300 IU/kg of WinRho®SDF may also be at an increased risk of developing increased hemolysis. Fatal outcomes associated with IVH and its complications have occurred most frequently in patients of advanced age (age over 65) with co-morbid conditions.

Given the prevalence of co-morbid conditions and concomitant drug therapy in geriatric patients, consider starting at the low end of the dosing range when using WinRho®SDF in this population.

10 OVERDOSAGE

Treatment of ITP and Suppression of Rh Isoimmunization

In post-marketing spontaneous reporting, there has been a limited number of medication error reports related to dosage calculations in which higher doses than that recommended for WinRho®SDF were administered (doses > 60 mcg/kg). Signs and laboratory findings of overdosage in Rh positive (ITP) patients have included hemoglobin decreases in excess of 1.2 g/dL. For the suppression of Rh isoimmunization, hemolytic reactions have been reported in cases of mis-matched blood transfusions where very large doses of WinRho®SDF were administered.

In one ITP case report that involved an overdose due to confusion between mcg and international unit (IU), a patient with significant co-morbidities developed IVH and had a fatal outcome. In the event of overdose, monitor patients closely for signs and symptoms of hemolysis and initiate symptomatic and supportive treatment.

11 DESCRIPTION

WinRho®SDF is a sterile, liquid gamma globulin (IgG) fraction containing antibodies to the Rho(D) antigen (D antigen). WinRho®SDF is to be administered intravenously for the treatment of ITP and either intravenously or intramuscularly for the suppression of Rh isoimmunization.

WinRho®SDF is prepared from human plasma by an anion-exchange column chromatography method. The manufacturing process includes two steps implemented specifically for viral clearance. The solvent detergent treatment step (using tri-n-butyl phosphate and octoxynol) is effective in inactivating lipid enveloped viruses such as hepatitis B, hepatitis C, and HIV. Virus filtration, using a 20N virus filter, is effective in the removal of some non-lipid enveloped viruses. These two processes are designed to increase product safety by reducing the risk of transmission of enveloped and non-enveloped viruses, respectively. In addition to the two specific steps, the anion-exchange chromatography step contributes to the removal of small non-lipid enveloped viruses.

The inactivation and reduction of known enveloped and non-enveloped model viruses were validated in laboratory studies as summarized in Table 6.

Table 6: Virus Reduction Values Obtained Through Validation Studies
 | Enveloped |  |  | Non-Enveloped
Genome | RNA |  | DNA | RNA |  | DNA
Virus | HIV-1 | BVDV | PRV | HAV | EMC | MMV |  | PPV
Family | retro | flavi | herpes | picorna |  | parvo
Size (nm) | 80-100 | 50-70 | 120-200 | 25-30 | 30 | 20-25 |  | 18-24
Anion Exchange Chromatography (partitioning) | n.e. |  |  | 2.3 | n.e. | 3.4 |  | n.e.
20N Filtration (size exclusion) | ≥ 4.7 | ≥ 3.5 | ≥ 5.6* | n.e. | 4.8 | n.e. |  | 4.1
Solvent/Detergent (inactivation) | ≥ 4.7 | ≥ 7.3 | ≥ 5.5 | n.e.
Total Reduction (log10) | ≥ 9.4 | ≥ 10.8 | ≥ 11.1 | 2.3 | 4.8 | 3.4 | 4.1
* The PRV was retained by the 0.1 μm pre-filter during the virus validation. Since manufacturing employs a 0.1 μm pre-filter before the 20N filter, the claim of ≥5.6 reduction is considered applicable.
Abbreviations:
HIV-1: human immunodeficiency virus-1; relevant virus for human immunodeficiency virus-1 and model for HIV-2.
BVDV: bovine viral diarrhea virus; model virus for hepatitis C virus (HCV) and West Nile virus (WNV)
PRV: pseudorabies virus; model for large enveloped DNA viruses, including herpes
HAV: human hepatitis A virus; relevant virus for HAV and model for small non-enveloped viruses in general
EMC: encephalomyocarditis virus; model for HAV and for small non-enveloped viruses in general
MMV: murine minute virus; model for human parvovirus B19 and for small non-enveloped viruses in general
PPV: porcine parvovirus; model for human parvovirus B19 and for small non-enveloped viruses in general
n.e.: not evaluated

The product potency is expressed in international units (IU) by comparison to the World Health Organization (WHO) standard. In the past, a full dose of Rho(D) Immune Globulin (Human) has traditionally been referred to as a “300 microgram (mcg)” dose. Potency and dosing recommendations are now expressed in IU by comparison to the WHO anti-Rho(D) standard. The conversion of mcg to IU is: 1 mcg = 5 IU. A 1,500 IU (300 mcg) vial contains sufficient anti-Rho(D) to effectively suppress the immunizing potential of approximately 17 mL of Rho(D) (D-positive) RBCs.

The liquid formulation is stabilized with 10% maltose and 0.03% polysorbate 80. There are no preservatives in the formulation. WinRho®SDF does not contain mercury. This product contains ≤ 40 mcg/mL IgA.

12 CLINICAL PHARMACOLOGY

12.1 Mechanism of Action

Treatment of ITP

WinRho®SDF has been shown to increase platelet counts in non-splenectomized, Rho(D)-positive patients with ITP. Platelet counts usually rise within one to two days and peak within seven to 14 days after initiation of therapy. The mechanism of action is not completely understood, but is thought to be due to the formation of anti-Rho(D)-coated RBC complexes, which are preferentially removed by the reticuloendothelial system, particularly the spleen. This results in Fc receptor blockade, thus sparing antibody-coated platelets.^9,10

Suppression of Rh Isoimmunization

The mechanism by which Rho(D) immune globulin suppresses immunization to Rho(D)-positive RBCs is not completely understood.

WinRho®SDF when administered within 72 hours of a full-term delivery of a Rho(D)-positive infant by a Rho(D) negative mother will reduce the incidence of Rh isoimmunization from 12-13% to 1-2%. The 1-2% is, for the most part, due to isoimmunization during the last trimester of pregnancy. When treatment is given both antenatally, at 28-weeks gestation, and postpartum, the Rh immunization rate drops to about 0.1%.^13,14

When 600 IU (120 mcg) of WinRho®SDF is administered to pregnant women, passive anti-Rho(D) antibodies are not detectable in the circulation for more than six weeks and therefore a dose of 1,500 IU (300 mcg) should be used for antenatal administration.

12.2 Pharmacodynamics

In a clinical study with Rho(D)-negative volunteers (nine males and one female), Rho(D)-positive RBCs were completely cleared from the circulation within 8 hours of intravenous administration of WinRho®SDF. There was no indication of Rh isoimmunization of these subjects at six months after the clearance of the Rho(D)-positive RBCs.

12.3 Pharmacokinetics

IM versus IV Administration (Lyophilized Powder)

In a clinical study involving Rho(D)-negative volunteers, two subjects received 600 IU (120 mcg) WinRho®SDF by intravenous (IV) administration and two subjects received this dose by intramuscular (IM) administration. Peak levels (36 to 48 ng/mL) were reached within two hours of IV administration and peak levels (18 to 19 ng/mL) were reached at five to 10 days after IM administration. Although no statistical comparisons were made, the calculated areas under the curve were comparable for both routes of administration. The t½for anti-Rho(D) was about 24 days following IV administration and about 30 days following IM administration.

Lyophilized Powder versus Liquid Formulation

In two comparative pharmacokinetics studies, 101 volunteers were administered the liquid or lyophilized formulation of WinRho®SDF intravenously (n=41) or intramuscularly (n=60). The formulations were bioequivalent following IV administration based on area under the curve to 84 days and had comparable pharmacokinetics following IM administration. The average peak concentrations (Cmax) of anti-Rho(D) for both formulations were comparable following IV or IM administration and occurred within 30 minutes or 2-4 days of administration, respectively. Both formulations also had similar elimination half-lives (t½) following IV or IM administration.

14 CLINICAL STUDIES

14.1 Treatment of ITP

Efficacy was documented in four subgroups of patients with ITP:

Childhood Chronic ITP

In an open-label, single arm, multicenter study, 24 non-splenectomized, Rho(D)-positive children with ITP of greater than six-months duration were treated initially with 250 IU/kg (50 mcg/kg) WinRho®SDF [125 IU/kg (25 mcg/kg) on days 1 and 2, with subsequent doses ranging from 125 to 275 IU/kg (25 to 55 mcg/kg)]. Response was defined as a platelet increase to at least 50,000/mm^3and a doubling of the baseline. Nineteen of 24 patients responded for an overall response rate of 79%, an overall mean peak platelet count of 229,400/mm^3(range 43,300 to 456,000), and a mean duration of response of 36.5 days (range 6 to 84).^15

Childhood Acute ITP

A multicenter, randomized, controlled trial comparing WinRho®SDF to high dose and low dose Immune Globulin Intravenous (Human) (IGIV) and prednisone was conducted in 146 non-splenectomized, Rho(D)-positive children with acute ITP and platelet counts less than 20,000/mm^3. Of 38 patients receiving WinRho®SDF [125 IU/kg (25 mcg/kg) on days 1 and 2], 32 patients (84%) responded (platelet count ≥ 50,000/mm^3) with a mean peak platelet count of 319,500/mm^3(range 61,000 to 892,000), with no statistically significant differences compared to other treatment arms. The mean times to achieving ≥ 20,000/mm^3or ≥ 50,000/mm^3platelets for patients receiving WinRho®SDF were 1.9 and 2.8 days respectively. When comparing the different therapies for time to platelet count ≥ 20,000/mm^3or ≥ 50,000/mm^3, no statistically significant differences among treatment groups were detected, with a range of 1.3 to 1.9 days and 2.0 to 3.2 days, for IGIV and prednisone respectively.^16,17

Adult Chronic ITP

Twenty-four non-splenectomized Rho(D)-positive adults with ITP of greater than six-months duration and platelet counts < 30,000/mm^3or requiring therapy were enrolled in a single-arm, open-label trial were treated with 100 to 375 IU/kg (20 to 75 mcg/kg) WinRho®SDF [mean dose 231 IU/kg (46.2 mcg/kg)]. Twenty-one of 24 patients responded (increase ≥ 20,000/mm^3) during the first two courses of therapy for an overall response rate of 88% with a mean peak platelet count of 92,300/mm^3(range 8,000 to 229,000).^18,19

ITP Secondary to HIV Infection

Eleven children and 52 adults, who were non-splenectomized and Rho(D)-positive, with all Walter Reed classes of HIV infection and ITP, with initial platelet counts of ≤ 30,000/mm^3or requiring therapy, were treated with 100 to 375 IU/kg (20 to 75 mcg/kg) WinRho®SDF in an open label trial. WinRho®SDF was administered for an average of 7.3 courses (range 1 to 57) over a mean period of 407 days (range 6 to 1,952). Fifty-seven of 63 patients responded (increase ≥ 20,000/mm^3) during the first six courses of therapy for an overall response rate of 90%. The overall mean change in platelet count for six courses was 60,900/mm^3(range -2,000 to 565,000), and the mean peak platelet count was 81,700/mm^3(range 16,000 to 593,000).^18-20

14.2 Suppression of Rh Isoimmunization

A study was conducted in 1,186 non-sensitized, Rho(D)-negative pregnant women in cases in which the blood types of the fathers were Rho(D)-positive or unknown. WinRho®SDF was administered according to one of three regimens: 1) 93 women received 600 IU (120 mcg) at 28 weeks; 2) 131 women received 1,200 IU (240 mcg) each at 28 and 34 weeks; 3) 962 women received 1,200 IU (240 mcg) at 28 weeks. All women received a postnatal administration of 600 IU (120 mcg) if the newborn was found to be Rho(D)-positive. Of 1,186 women who received antenatal WinRho®SDF, 806 were given WinRho®SDF postnatal following the delivery of a Rho(D)-positive infant, of which 325 women underwent testing at six months after delivery for evidence of Rh isoimmunization. Of these 325 women, 23 would have been expected to display signs of Rh isoimmunization, however, none was observed (p <0.001 in a Chi-square test of significance of difference between observed and expected isoimmunization in the absence of WinRho®SDF).

15 REFERENCES

1. Provan D, et al.: International consensus report on the investigation and management of primary immune thrombocytopenia. Blood 2010; 115:168-186.
2. Gupta N, Ahmed I, Nissel-Horowitz S, Patel D, Mehrotra B. Intravenous gammaglobulin-associated acute renal failure. Am J Hematol 2001; 66:151-152
3. Dalakas MC. High-dose intravenous immunoglobulin and serum viscosity: risk of precipitating thromboembolic events. Neurology 1994; 44:223-226.
4. Woodruff RK, et al.: Fatal thrombotic events during treatment of autoimmune thrombocytopenia with intravenous immunoglobulin in elderly patients. Lancet 1986; 2:217-218.
5. Rushin J, Rumsey, DH, Ewing, CA, Sandler, SG. Detection of multiple passively acquired alloantibodies following infusions of IV Rh immune globulins. Transfusion Vol. 40, May 2000.
6. Rizk A, et al.: Transfusion-related acute lung injury after the infusion of IVIG. Transfusion 2001; 41:264-8.
7. Gaines AR. Acute onset hemoglobinemia and/or hemoglobinuria and sequalae following Rho(D) immune globulin intravenous administration in immune thrombocytopenic purpura patients. Blood 2000; 95(8): 2523-2529.
8. Gaines AR. Disseminated intravascular coagulation associated with acute hemoglobinemia and/or hemoglobinuria following Rho(D) immune globulin intravenous administration for immune thrombocytopenic purpura. Blood 2005; 106(5); 1532-7.
9. Ballow, M: Mechanisms of action of intravenous immunoglobulin therapy and potential use in autoimmune connective tissue diseases. Cancer. 1991; 68:1430-1436.
10. Kniker, WT: Immunosuppressive agents, γ-globulin, immunomodulation, immunization, and apheresis. J. Aller. Clin. Immunol. 1989; 84:1104-1106.
11. Lazarus AH, Crow AR. Mechanism of action of IVIG and anti-D in ITP. Transfus Apheresis Sci 2003; 28:249-255.
12. Bowman JM. The prevention of Rh immunization. Transfus Med Rev 1988; 2(3):129-150
13. Bowman, JM, and Pollock, JM: Failures of intravenous Rh immune globulin prophylaxis: An analysis of the reasons for such failures. Trans. Med. Rev. 1987; 1:101-111.
14. Bowman, JM: Antenatal suppression of Rh alloimmunization. Clin Obstet. & Gynec. 1991; 34:296-303.
15. Andrew, M, et al.: A multicenter study of the treatment of childhood chronic idiopathic thrombocytopenic purpura with anti-D. J Pediatrics 1992; 120:522-527.
16. Blanchette, V, et al.: Randomised trial of intravenous immunoglobulin G, intravenous anti-D, and oral prednisone in childhood acute immune thrombocytopenic purpura. Lancet 1994; 344: 703-707.
17. Zunich KM, et al. Intravenous anti-D immunoglobulin for childhood acute immune thrombocytopenic purpura. Lancet 1995; 346:1363-5.
18. Scaradavou A, et al.: Intravenous anti-D treatment of immune thrombocytopenic purpura: experience in 272 patients. Blood 1997; 89:2689-700.
19. Bussel, JB, et al.: Intravenous anti-D treatment of immune thrombocytopenic purpura: Analysis of efficacy, toxicity, and mechanism of effect. Blood 1991; 77: 1884-1893.
20. Zunich KM, et al.: Treatment of human immunodeficiency virus-related thrombocytopenia with intravenous anti-rhesus D immunoglobulin. Clin Infect Dis 1996; 22:1129-30.

16 HOW SUPPLIED/STORAGE AND HANDLING

- Store at 2 to 8°C (36 to 46°F)
- Do not freeze
- Do not use after expiration date
- Protect from light

WinRho®SDF is available in packages containing:

NDC Number | Product Description
49591-312-51 | A carton containing a single dose vial of 600 IU (120 mcg) anti-Rho(D) IGIV and a package insert
49591-330-51 | A carton containing a single dose vial of 1,500 IU (300 mcg) anti-Rho(D) IGIV and a package insert
49591-350-51 | A carton containing a single dose vial of 2,500 IU (500 mcg) anti-Rho(D) IGIV and a package insert
49591-310-51 | A carton containing a single dose vial of 5,000 IU (1,000 mcg) anti-Rho(D) IGIV and a package insert
49591-300-51 | A carton containing a single dose vial of 15,000 IU (3,000 mcg) anti-Rho(D) IGIV and a package insert

17 PATIENT COUNSELING INFORMATION

Information for Patients

See FDA-Approved Patient Labeling

- ITP and Suppression of Rh Isoimmunization
  - Inform patients of the early signs of hypersensitivity reactions to WinRho®SDF including hives, generalized urticaria, chest tightness, wheezing, hypotension, and anaphylaxis.
  - Advise patients to notify their physicians if they experience any of the above symptoms.
- Blood Glucose Monitoring
  - Advise patients that the maltose contained in WinRho®SDF can interfere with some types of blood glucose monitoring systems.
  - Advise patients to use only testing systems that are glucose specific for monitoring blood glucose levels as the interference of maltose could result in falsely elevated glucose readings. This could lead to untreated hypoglycemia or to inappropriate insulin administration, resulting in life-threatening hypoglycemia.
- Transmittable Infectious Agents
  - Inform patients that WinRho®SDF is prepared from human plasma and may contain infectious agents (e.g., viruses and, theoretically, the CJD agent) that can cause disease. The risk that such products will transmit an infectious agent has been reduced by screening plasma donors for prior exposure to certain viruses, by testing for the presence of current virus infections, and by inactivating and/or removing certain viruses during manufacturing.
  - Advise patients to report any symptoms that concern them and that may be related to viral infections.
- Live Virus Vaccines
  - Advise patients that WinRho®SDF may impair the effectiveness of certain live virus vaccines (e.g., measles, rubella, mumps, and varicella).
  - Instruct patients to notify their treating physician of this potential interaction when they are receiving vaccinations.
- Immune Thrombocytopenic Purpura (ITP)
  - Instruct patients being treated with WinRho®SDF for ITP to immediately reportsymptoms of intravascular hemolysis including back pain, shaking chills, fever, discolored urine, decreased urine output, sudden weight gain, fluid retention/edema, and/or shortness of breath to their physicians.
  - Prior to discharge, instruct patients to continue to self-monitor for the signs and symptoms of IVH over 72 hours, especially for discoloration of urine, and to seek medical attention immediately in the event that signs/symptoms of IVH occur following WinRho® SDF administration.
- Laboratory Tests

Assess renal function in patients judged to be at an increased risk of developing acute renal failure, including measurement of BUN and serum creatinine, before the initial infusion of WinRho®SDF.

17.1 FDA Approved Patient Labeling – (Patient Prescribing Information)

WinRho® SDF

[pronounced win – row –S-D-F]

You should read this leaflet carefully each time before you are scheduled to receive a treatment for your Immune Thrombocytopenic Purpura (ITP) with WinRho® SDF. This letter is a summary of the important information you need to know about your medicine, and does not take the place of talking with your doctor and does not contain all of the information available about WinRho®SDF. If you have any questions after reading this leaflet, make sure you ask your doctor or nurse.

1. What is the most important information I should know about WinRho® SDF?

Some patients taking WinRho®SDF for immune thrombocytopenic purpura (ITP) have had severe, life threatening bleeding and clotting problems. For this reason, you need to remain under observation for at least 8 hours following each treatment with WinRho® SDF and your doctor will ask you to take blood and urine tests before and after infusion with WinRho® SDF.

Some patients taking WinRho®SDF have had problems with their kidneys and other organs.

Problems usually occur within 4 to 8 hours after getting an infusion. Tell your doctor or healthcare provider right away if you have any of the following signs or symptoms after getting a WinRho®SDF infusion:

- back pain
- shaking
- chills
- fever
- dark or oddly colored urine
- decreased urination
- swelling or sudden weight gain
- shortness of breath
- rash
- dizziness

Continue monitoring for these signs and symptoms for 72 hours after each treatment with WinRho® SDF.

WinRho®SDF contains maltose, which can give false readings on some glucose testing meters. If you are diabetic, ask your doctor what types of glucose testing meters can be used safely while you are getting WinRho®SDF.

2. What is WinRho® SDF?

WinRho®SDF is a protein product, called an “immune globulin,” which is made from human plasma. It has antibodies to the “D” antigen that people with “Rh-positive” blood have in their blood.

WinRho®SDF is used to increase the number of platelets in the blood of Rh-positive people who have a problem called immune thrombocytopenic purpura (ITP). People with ITP bruise and bleed easily because they have a very low number of platelets in their blood.

WinRho®SDF is also used to treat Rh-negative girls and women who need a blood transfusion using Rh-positive blood and/or are carrying a Rh-positive baby.

3. Who should not use WinRho® SDF?

You should not use WinRho®SDF for any treatment if you:

- have ever had a severe allergic reaction (such as trouble breathing, hives, passing out) after getting any blood product or blood product transfusion.
- have an immune globulin A (IgA) deficiency.

You should not use WinRho®SDF for treatment of ITP if you:

- have Rh-negative blood.
- have had your spleen removed.
- have a problem called “autoimmune hemolytic anemia.”
- have other pre-existing bleeding problems.

4. How will I get WinRho® SDF?

Your doctor will give you WinRho®SDF as an injection into your vein. For the treatment of ITP, it will usually take 3 to 5 minutes for an injection. Your doctor will decide if you need one or more injections.

For protection against Rh-positive blood, your doctor may decide to give you WinRho® SDF as a shot in your arm or thigh.

5. What should I avoid while using WinRho® SDF?

WinRho®SDF may interfere with your immune response to routine immunizations. Tell your doctor if you have recently been vaccinated or are planning to be vaccinated.

WinRho®SDF can interfere with certain blood tests. It is important to tell the person taking your blood and the doctor that you got WinRho®SDF.

6. What are the possible or reasonably likely side effects of WinRho® SDF?

The most common side effects of WinRho®SDF are

- headache
- chills
- fever
- weakness
- diarrhea
- nausea and vomiting
- achy muscles
- feeling light-headed or dizziness
- fainting
- flushing
- rash
- sweating

Tell your doctor right away if you have:

- a fever over 100oF
- shaking or chills that continue or get worse
- a painful lump or swelling (because this may be a sign of a blood clot)
- bruising that is increasing in diameter (because this may be a sign of a clotting problem)
- oddly colored urine
- trouble urinating
- severe back pain
- severe abdominal pain
- swelling, especially around the ankles
- hives
- shortness of breath

Talk to your doctor about any side effects that concern you.

Additional prescribing information is available to healthcare professionals.

7. What other information do I need to know about WinRho® SDF?

WinRho®SDF is made from human plasma. Donors are carefully screened and the plasma is carefully cleaned, but it does have a very small risk of giving you viruses from the donor. Talk to your doctor if you have any symptoms that concern you.

You may report side effects to Kamada at 1-866-916-0077 or FDA's MedWatch reporting system by phone (1-800-FDA-1088)

WinRho®SDF [Rho(D) Immune Globulin Intravenous (Human)] Sterile Solution for Injection and any and all Kamada brand, product, service and feature names, logos, slogans are trademarks or registered trademarks of Kamada. All rights reserved.

Distributed by:

Kamada Inc.
Hoboken, NJ 07030

US License No. 1826

Principal Display Panel – 1500 IU Carton Label

NDC 49591-330-51

Rh 0 (D) Immune Globulin
Intravenous (Human)

WinRho® SDF Liquid

1500 international units
(300 mcg)

Target Vol.: 1.3 mL

FOR INTRAVENOUS
OR INTRAMUSCULAR
ADMINISTRATION

Rx only

KAMADA

Principal Display Panel – 1500 IU Vial Label

NDC 49591-330-11

Rh O (D) Immune Globulin
Intravenous (Human)

WinRho® SDF Liquid

1500 international units
(300 mcg)

Target Vol.: 1.3 mL

Principal Display Panel – 2500 IU Carton Label

NDC 49591-350-51

Rh 0 (D) Immune Globulin
Intravenous (Human)

WinRho® SDF Liquid

2500 international units
(500 mcg)

Target Vol.: 2.2 mL

FOR INTRAVENOUS
OR INTRAMUSCULAR
ADMINISTRATION

Rx only

KAMADA

Principal Display Panel – 2500 IU Vial Label

NDC 49591-350-02

Rh O (D) Immune Globulin
Intravenous (Human)

WinRho® SDF Liquid

2500 international units
(500 mcg)

Target Vol.: 2.2 mL

Principal Display Panel – 5000 IU Carton Label

NDC 49591-310-51

Rh 0 (D) Immune Globulin
Intravenous (Human)

WinRho® SDF Liquid

5000 international units
(1000 mcg)

Target Vol.: 4.4 mL

FOR INTRAVENOUS
OR INTRAMUSCULAR
ADMINISTRATION

Rx only

KAMADA

Principal Display Panel – 5000 IU Vial Label

NDC 49591-310-04

RhO(D) Immune Globulin
Intravenous (Human)

WinRho® SDF Liquid

5000 international units
(1000 mcg)

Target Vol.: 4.4 mL

Principal Display Panel – 15000 IU Carton Label

NDC 49591-300-51

Rh 0 (D) Immune Globulin
Intravenous (Human)

WinRho® SDF Liquid

15000 international units
(3000 mcg)

Target Vol.: 13 mL

FOR INTRAVENOUS
OR INTRAMUSCULAR
ADMINISTRATION

Rx only

KAMADA

Principal Display Panel – 15000 IU Vial Label

NDC 49591-300-13

Rh O (D) Immune Globulin
Intravenous (Human)

WinRho® SDF Liquid

15000 international units
(3000 mcg)

Target Vol.: 13.0 mL